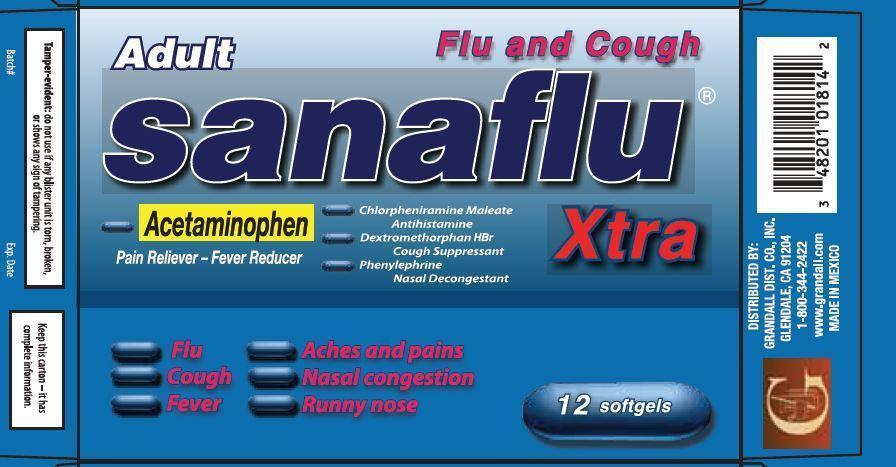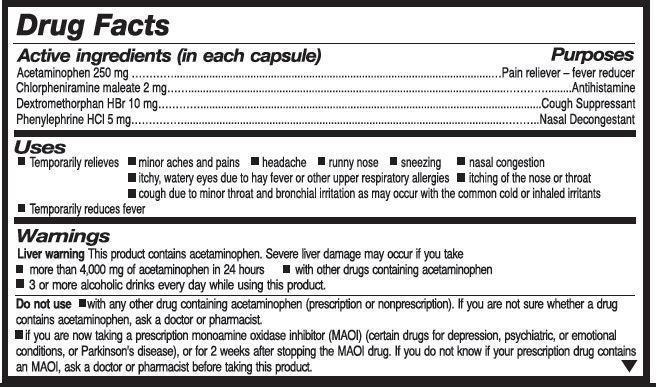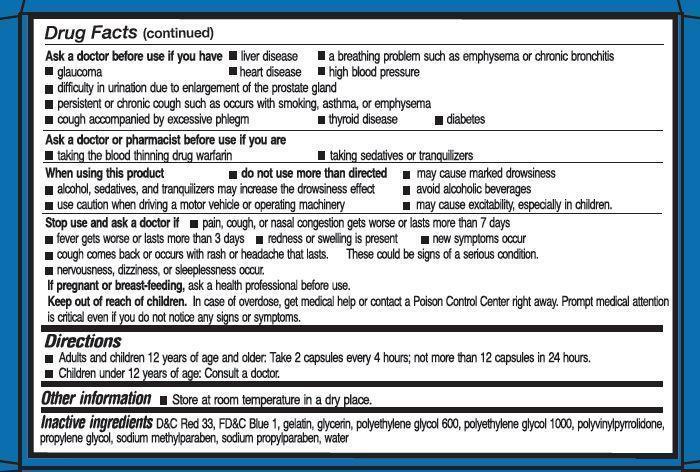 DRUG LABEL: Sanaflu Xtra
NDC: 48201-001 | Form: CAPSULE, GELATIN COATED
Manufacturer: GRANDALL DISTRIBUTING, LLC
Category: otc | Type: HUMAN OTC DRUG LABEL
Date: 20251028

ACTIVE INGREDIENTS: DEXTROMETHORPHAN HYDROBROMIDE 10 mg/1 1; PHENYLEPHRINE HYDROCHLORIDE 5 mg/1 1; ACETAMINOPHEN 250 mg/1 1; CHLORPHENIRAMINE MALEATE 2 mg/1 1
INACTIVE INGREDIENTS: METHYLPARABEN SODIUM; PROPYLPARABEN SODIUM; WATER; D&C RED NO. 33; FD&C BLUE NO. 1; GELATIN; GLYCERIN; POLYETHYLENE GLYCOL 600; POLYETHYLENE GLYCOL 1000; PROPYLENE GLYCOL

Grandall (as PLD) - Sanaflu Xtra (48201-001)

Active ingredients (in each capsule)

Acetaminophen 250 mg

Chlorpheniramine maleate 2 mg

Dextromethorphan HBr 10 mg

Phenylephrine HCl 5 mg

Purposes

Pain reliever - fever reducer

Antihistamine

Cough Suppressant

Nasal Decongestant

Uses

- Temporarily relives
- minor aches and pains
- headache
- runny nose
- sneezing
- nasal congestion
- itchy, watery eyes due to hay fever or other upper respiratory allergies
- itching of the nose or throat
- cough due to minor throat and bronchial irritation as may occur with the common cold ro inhaled irritants
- Temperarily reduces fever

Warnings

Liver warningThis product contains acetaminophen. Severe liver damage may occur if you take

- more than 4,000 mg of acetaminophen in 24 hours
- with other drugs containing acetaminophen
- 3 or more alcoholic drinks every day while using this product.

Do not use

- with any other drug containing acetaminophen (prescription or nonprescription). If you are not sure whether a drug contains acetaminophen, ask a doctor or pharmacist.
- if you are now taking a prescription monamine oxidase inhibitor (MAOI) (certain drugs for depression, psychiatric, or emotional conditions, or Parkinson's disease), or for 2 weeks after stopping the MAOI drug. If you do not know if your prescription drug contains an MAOI, ask a doctor or pharmacist before taking this product.

Ask a doctor before use if you have

- liver disease
- a breathing problem such as emphysema or chronic bronchitis
- glaucoma
- heart disease
- high blood pressure
- difficulty in urination due to enlargement of the prostate gland
- persistant or chrnoic cough such as occurs with smoking, asthma, or emphysema
- cough accompanied by excessive phlegm
- thyroid disease
- diabetes

Ask a doctor or pharmacist before use if you are

- taking the blood thinning drug warfarin
- taking sedativies or tranquilizers

When using this product

- do not use more than directed
- may cause marked drowsiness
- alcohol, sedativies, and tranquilizers may increase the drowsiness effect
- avoid alcoholic beverages
- use caution when driving a motor vehicle or operating machinery
- may cause excitability, especially in children.

Stop use and ask a doctor if

- pain, cough, or nasal congestion gets worse or lasts more than 7 days
- fever gets worse or lasts more than 3 days
- redness or swelling is present
- new symptoms occur
- cough comes back or occurs with rash or headache that lasts. These could be signs of a serious condition.
- nervousness, dizziness, or sleeplessness occur.

If pregnant or breast-feeding,

ask a health professional before use.

Keep out of reach of children.

In case of overdose, get medical help or contact a Poison Control Center right away. Prompt medical attention is critial even if you do not notice any signs or symptoms.

Directions

- Adults and children 12 years of age and older: Take 2 capsules every 4 hours; not more than 12 capsules in 24 hours.
- Children under 12 years of age: Consult a doctor.

Other information

- Store at room temperature in a dry place.

Inactive ingredients

D&C Red 33, FD&C Blue 1, gelatin, glycerin, polyethylene glycol 600, polyethylene glycol 1000, polyvinylpyrrolidone, propylene glycol, sodium methylparaben, sodium propylparaben, water